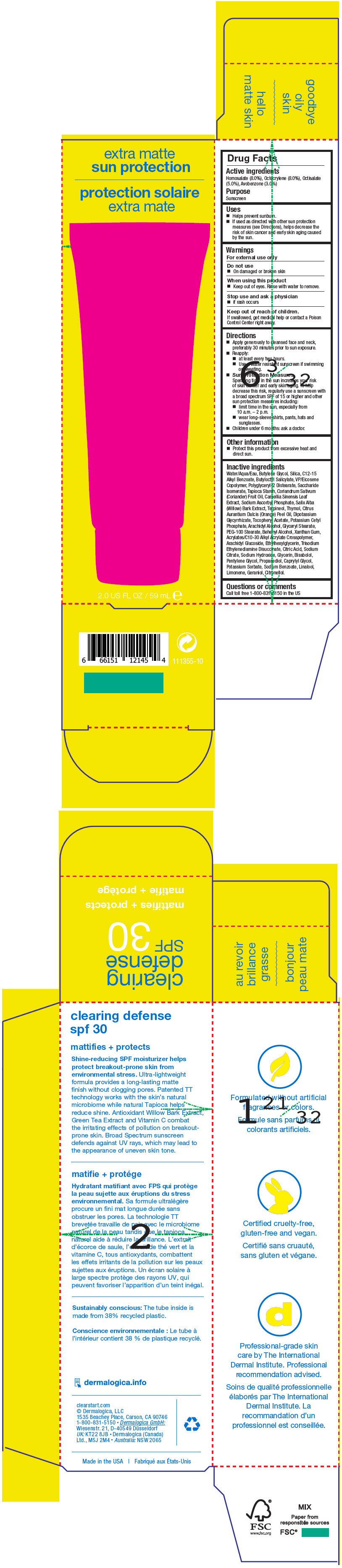 DRUG LABEL: Clearing Defense SPF 30
NDC: 68479-807 | Form: LOTION
Manufacturer: Dermalogica, Inc.
Category: otc | Type: HUMAN OTC DRUG LABEL
Date: 20241226

ACTIVE INGREDIENTS: Avobenzone 30 mg/1 mL; Homosalate 80 mg/1 mL; Octisalate 50 mg/1 mL; Octocrylene 80 mg/1 mL
INACTIVE INGREDIENTS: Water; Butylene Glycol; Silicon Dioxide; Butyloctyl Salicylate; ALKYL (C12-15) BENZOATE; VINYLPYRROLIDONE/EICOSENE COPOLYMER; Glycerin; Polyglyceryl-2 Stearate; Saccharide Isomerate; STARCH, TAPIOCA; CORIANDER OIL; GREEN TEA LEAF; Sodium Ascorbyl Phosphate; SALIX ALBA BARK; Terpineol; Thymol; ORANGE OIL, COLD PRESSED; GLYCYRRHIZINATE DIPOTASSIUM; Potassium Sorbate; Potassium Cetyl Phosphate; Arachidyl Alcohol; Glyceryl Stearate SE; PEG-100 Stearate; DOCOSANOL; LEVOMENOL; Xanthan Gum; ETHYL ACRYLATE/METHACRYLIC ACID/STEARETH-20 METHACRYLATE COPOLYMER; Arachidyl Glucoside; Ethylhexylglycerin; .ALPHA.-TOCOPHEROL ACETATE; Trisodium Ethylenediamine Disuccinate; CITRIC ACID MONOHYDRATE; SODIUM CITRATE, UNSPECIFIED FORM; Sodium Hydroxide; Pentylene Glycol; Propanediol; Caprylyl Glycol; Sodium Benzoate

Clearing Defense SPF 30

Drug Facts

Active ingredients

Homosalate (8.0%), Octocrylene (8.0%), Octisalate (5.0%), Avobenzone (3.0%)

Purpose

Sunscreen

Uses

- Helps prevent sunburn.
- If used as directed with other sun protection measures (see Directions), helps decrease the risk of skin cancer and early skin aging caused by the sun.

Warnings

For external use only

Do not use

- On damaged or broken skin

When using this product

- Keep out of eyes. Rinse with water to remove.

Stop use and ask a physician

- if rash occurs

Keep out of reach of children.

If swallowed, get medical help or contact a Poison Control Center right away.

Directions

- Apply generously to cleansed face and neck, preferably 30 minutes prior to sun exposure.
- Reapply:
  - at least every two hours.
  - Use a water resistant sunscreen if swimming or sweating.
- Sun Protection Measures
  Spending time in the sun increases your risk of skin cancer and early skin aging. To help decrease this risk, regularly use a sunscreen with a broad spectrum SPF of 15 or higher and other sun protection measures including:
  - limit time in the sun, especially from 10 a.m. – 2 p.m.
  - wear long-sleeve shirts, pants, hats and sunglasses.
- Children under 6 months: ask a doctor.

Other information

- Protect this product from excessive heat and direct sun.

Inactive ingredients

Water/Aqua/Eau, Butylene Glycol, Silica, C12-15 Alkyl Benzoate, Butyloctyl Salicylate, VP/Eicosene Copolymer, Polyglyceryl-2 Distearate, Saccharide Isomerate, Tapioca Starch, Coriandrum Sativum (Coriander) Fruit Oil, Camellia Sinensis Leaf Extract, Sodium Ascorbyl Phosphate, Salix Alba (Willow) Bark Extract, Terpineol, Thymol, Citrus Aurantium Dulcis (Orange) Peel Oil, Dipotassium Glycyrrhizate, Tocopheryl Acetate, Potassium Cetyl Phosphate, Arachidyl Alcohol, Glyceryl Stearate, PEG-100 Stearate, Behenyl Alcohol, Xanthan Gum, Acrylates/C10-30 Alkyl Acrylate Crosspolymer, Arachidyl Glucoside, Ethylhexylglycerin, Trisodium Ethylenediamine Disuccinate, Citric Acid, Sodium Citrate, Sodium Hydroxide, Glycerin, Bisabolol, Pentylene Glycol, Propanediol, Caprylyl Glycol, Potassium Sorbate, Sodium Benzoate, Linalool, Limonene, Geraniol, Citronellol.

Questions or comments

Call toll free 1-800-831-5150 in the US

PRINCIPAL DISPLAY PANEL - 59 mL Tube Carton

extra matte
sun protection

2.0 US FL OZ / 59 mL ℮